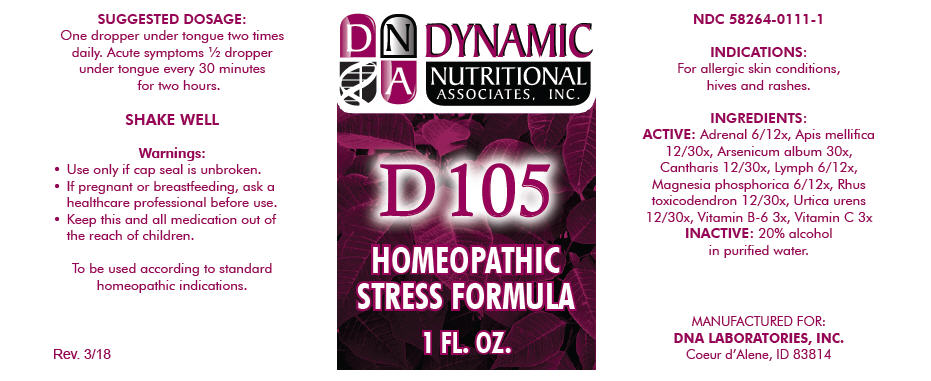 DRUG LABEL: D-105
NDC: 58264-0111 | Form: SOLUTION
Manufacturer: DNA Labs, Inc.
Category: homeopathic | Type: HUMAN OTC DRUG LABEL
Date: 20250113

ACTIVE INGREDIENTS: BOS TAURUS ADRENAL GLAND 6 [hp_X]/1 mL; APIS MELLIFERA 12 [hp_X]/1 mL; ARSENIC TRIOXIDE 30 [hp_X]/1 mL; LYTTA VESICATORIA 12 [hp_X]/1 mL; BOS TAURUS LYMPH VESSEL 6 [hp_X]/1 mL; MAGNESIUM PHOSPHATE, DIBASIC TRIHYDRATE 6 [hp_X]/1 mL; TOXICODENDRON PUBESCENS LEAF 12 [hp_X]/1 mL; URTICA URENS 12 [hp_X]/1 mL; PYRIDOXINE HYDROCHLORIDE 3 [hp_X]/1 mL; ASCORBIC ACID 3 [hp_X]/1 mL
INACTIVE INGREDIENTS: ALCOHOL; WATER

D-105

NDC 58264-0111-1

INDICATIONS

PURPOSE

For allergic skin conditions, hives and rashes.

INGREDIENTS

ACTIVE

Adrenal 6/12x, Apis mellifica 12/30x, Arsenicum album 30x, Cantharis 12/30x, Lymph 6/12x, Magnesia phosphorica 6/12x, Rhus toxicodendron 12/30x, Urtica urens 12/30x, Vitamin B-6 3x, Vitamin C 3x

INACTIVE

20% alcohol in purified water.

SUGGESTED DOSAGE

One dropper under tongue two times daily. Acute symptoms ½ dropper under tongue every 30 minutes for two hours.

STORAGE AND HANDLING

SHAKE WELL

Warnings

- Use only if cap seal is unbroken.

PREGNANCY OR BREAST FEEDING

- If pregnant or breastfeeding, ask a healthcare professional before use.

KEEP OUT OF REACH OF CHILDREN

- Keep this and all medication out of the reach of children.

To be used according to standard homeopathic indications.

PRINCIPAL DISPLAY PANEL - 1 FL. OZ. Bottle Label

DYNAMIC
NUTRITIONAL
ASSOCIATES, INC.

D 105

HOMEOPATHIC
STRESS FORMULA

1 FL. OZ.